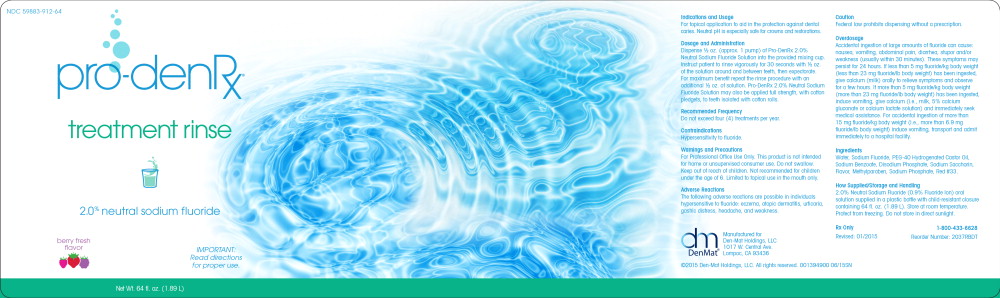 DRUG LABEL: Pro-Den Rx
NDC: 59883-912 | Form: RINSE
Manufacturer: Den-mat Holdings, Llc
Category: prescription | Type: HUMAN PRESCRIPTION DRUG LABEL
Date: 20190228

ACTIVE INGREDIENTS: SODIUM FLUORIDE 0.9 mg/1 mL
INACTIVE INGREDIENTS: WATER; POLYOXYL 40 HYDROGENATED CASTOR OIL; SODIUM BENZOATE; SODIUM PHOSPHATE, DIBASIC, ANHYDROUS; SACCHARIN SODIUM; METHYLPARABEN; SODIUM PHOSPHATE; D&C RED NO. 33

For topical application to aid in the protection against dental caries. Neutral pH is especially safe for crowns and restorations.

Dosage and Administration

Dispense ½ oz. (approx. 1 pump) of Pro-DenRx 2.0% Neutral Sodium Fluoride Solution into the provided mixing cup. Instruct patient to rinse vigorously for 30 seconds with ½ oz. of the solution around and between teeth, then expectorate. For maximum benefit repeat the rinse procedure with an additional ½ oz. of solution. Pro-DenRx 2.0% Neutral Sodium Fluoride Solution may also be applied full strength, with cotton pledgets, to teeth isolated with cotton rolls.

Recommended Frequency

Do not exceed four (4) treatments per year.

Contraindications

Hypersensitivity to fluoride.

Warnings and Precautions

For Professional Office Use Only. This product is not intended for home or unsupervised consumer use. Do not swallow. Keep out of reach of children. Not recommended for children under the age of 6. Limited to topical use in the mouth only.

Adverse Reactions

The following adverse reactions are possible in individuals hypersensitive to fluoride: eczema, atopic dermatitis, urticaria, gastric distress, headache, and weakness.

Caution

Federal law prohibits dispensing without a prescription.

Overdosage

Accidental ingestion of large amounts of fluoride can cause: nausea, vomiting, abdominal pain, diarrhea, stupor and/or weakness (usually within 30 minutes). These symptoms may persist for 24 hours. If less than 5 mg fluoride/kg body weight (less than 23 mg fluoride/lb body weight) has been ingested, give calcium (milk) orally to relieve symptoms and observe for a few hours. If more than 5 mg fluoride/kg body weight (more than 23 mg fluoride/lb body weight) has been ingested, induce vomiting, give calcium (i.e., milk, 5% calcium gluconate or calcium lactate solution) and immediately seek medical assistance. For accidental ingestion of more than 15 mg fluoride/kg body weight (i.e., more than 6.9 mg fluoride/lb body weight) induce vomiting, transport and admit immediately to a hospital facility.

Ingredients

Water, Sodium Fluoride, PEG-40 Hydrogenated Castor Oil, Sodium Benzoate, Disodium Phosphate, Sodium Saccharin, Flavor, Methylparaben, Sodium Phosphate, Red #33.

How Supplied/Storage and Handling

2.0% Neutral Sodium Fluoride (0.9% Fluoride Ion) oral solution supplied in a plastic bottle with child-resistant closure containing 64 fl. oz. (1.89 L). Store at room temperature. Protect from freezing. Do not store in direct sunlight.

Rx Only

Revised: 01/2015

1-800-433-6628

Reorder Number: 2037RBDT

Manufactured for

Den-Mat Holdings, LLC

1017 W. Central Ave.

Lompoc, CA 93436

©2015 Den-Mat Holdings, LLC. All rights reserved. 001394900 06/15SN

Principal Display Panel - 64 fl. oz. Bottle Label

NDC 59883-912-64

treatment rinse

2.0% neutral sodium fluoride

berry fresh flavor

IMPORTANT:
Read directions for proper use.

Net Wt. 64 fl. oz. (1.89 L)